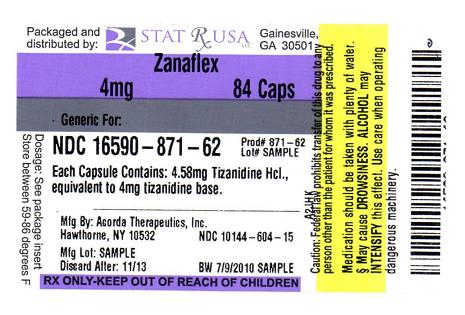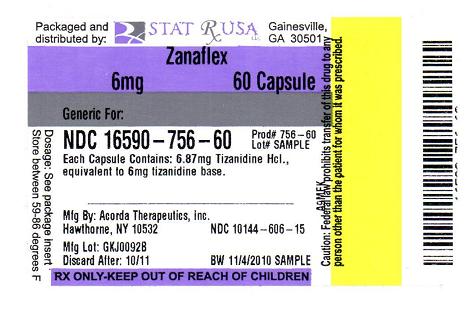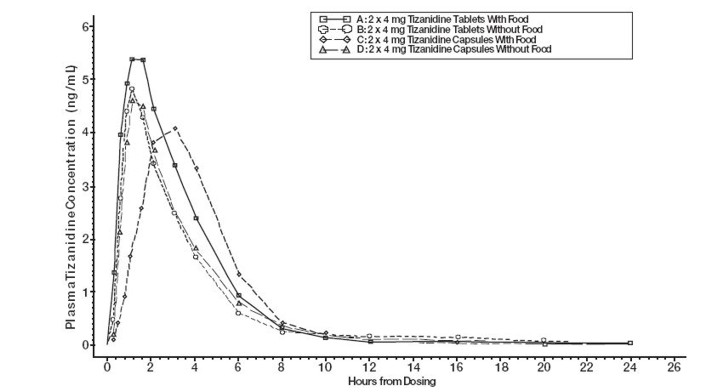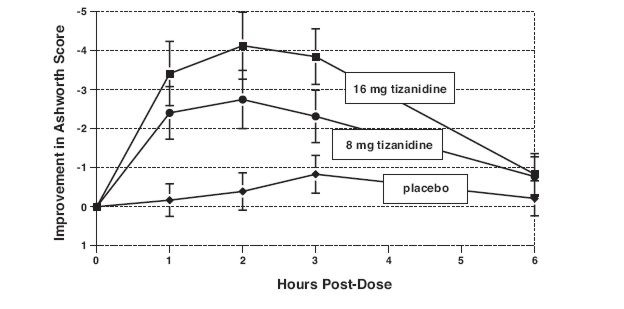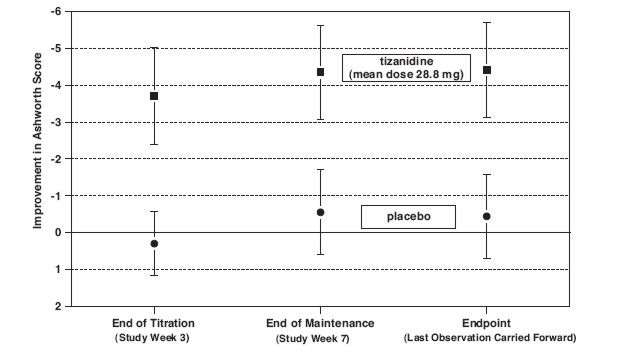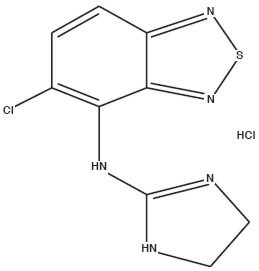 DRUG LABEL: ZANAFLEX
NDC: 16590-871 | Form: CAPSULE
Manufacturer: STAT RX USA LLC
Category: prescription | Type: HUMAN PRESCRIPTION DRUG LABEL
Date: 20110425

ACTIVE INGREDIENTS: TIZANIDINE HYDROCHLORIDE 4 mg/1 1
INACTIVE INGREDIENTS: HYDROXYMETHYL CELLULOSE; SILICON DIOXIDE; TITANIUM DIOXIDE; GELATIN

PHARMACOKINETIC DIFFERENCES BETWEEN ZANAFLEX CAPSULES® AND ZANAFLEX® TABLETS:

ZANAFLEX CAPSULES® ARE NOT BIOEQUIVALENT TO ZANAFLEX® TABLETS IN THE FED STATE. THE PRESCRIBER SHOULD BE THOROUGHLY FAMILIAR WITH THE COMPLEX EFFECTS OF FOOD ON TIZANIDINE PHARMACOKINETICS (see PHARMACOKINETICS and DOSAGE AND ADMINISTRATION).

DESCRIPTION

Zanaflex® (tizanidine hydrochloride) is a centrally acting α2-adrenergic agonist. Tizanidine HCl (tizanidine) is a white to off-white, fine crystalline powder, which is odorless or with a faint characteristic odor. Tizanidine is slightly soluble in water and methanol; solubility in water decreases as the pH increases. Its chemical name is 5-chloro-4-(2-imidazolin-2-ylamino)-2,1,3-benzothiodiazole hydrochloride. Tizanidine's molecular formula is C9H8ClN5S-HCl, its molecular weight is 290.2 and its structural formula is:

Zanaflex Capsules® are supplied as 2, 4, and 6 mg capsules and Zanaflex® tablets are supplied as 4 mg tablets for oral administration. Zanaflex Capsules® are composed of the active ingredient, tizanidine hydrochloride (2.29 mg equivalent to 2 mg tizanidine base, 4.58 mg equivalent to 4 mg tizanidine base, and 6.87 mg equivalent to 6 mg tizanidine base), and the inactive ingredients, hydroxypropyl methyl cellulose, silicon dioxide, sugar spheres, titanium dioxide, gelatin, and colorants.

Zanaflex® tablets are composed of the active ingredient, tizanidine hydrochloride (4.58 mg equivalent to 4 mg tizanidine base), and the inactive ingredients, silicon dioxide colloidal, stearic acid, microcrystalline cellulose and anhydrous lactose.

CLINICAL PHARMACOLOGY

MECHANISM OF ACTION

Tizanidine is an agonist at α2-adrenergic receptor sites and presumably reduces spasticity by increasing presynaptic inhibition of motor neurons. In animal models, tizanidine has no direct effect on skeletal muscle fibers or the neuromuscular junction, and no major effect on monosynaptic spinal reflexes. The effects of tizanidine are greatest on polysynaptic pathways. The overall effect of these actions is thought to reduce facilitation of spinal motor neurons. The imidazoline chemical structure of tizanidine is related to that of the anti-hypertensive drug clonidine and other α2-adrenergic agonists. Pharmacological studies in animals show similarities between the two compounds, but tizanidine was found to have one-tenth to one-fiftieth (1/50) of the potency of clonidine in lowering blood pressure.

PHARMACOKINETICS

Absorption and Distribution

Following oral administration, tizanidine is essentially completely absorbed. The absolute oral bioavailability of tizanidine is approximately 40% (CV = 24%), due to extensive first-pass hepatic metabolism. Tizanidine is extensively distributed throughout the body with a mean steady state volume of distribution of 2.4 L/kg (CV = 21%) following intravenous administration in healthy adult volunteers. Tizanidine is approximately 30% bound to plasma proteins.

Pharmacokinetics, Metabolism and Excretion

Tizanidine has linear pharmacokinetics over a dose of 1 to 20 mg. Tizanidine has a half-life of approximately 2.5 hours (CV=33%). Approximately 95% of an administered dose is metabolized. The primary cytochrome P450 isoenzyme involved in tizanidine metabolism is CYP1A2. Tizanidine metabolites are not known to be active; their half-lives range from 20 to 40 hours.

Following single and multiple oral dosing of ^14C-tizanidine, an average of 60% and 20% of total radioactivity was recovered in the urine and feces, respectively.

Pharmacokinetic differences between Zanaflex Capsules® and Zanaflex® Tablets

Zanaflex Capsules® and Zanaflex® tablets are bioequivalent to each other under fast conditions, but not under fed conditions.

A single dose of either two 4 mg tablets or two 4 mg capsules was administered under fed and fasting conditions in an open label, four period, randomized crossover study in 96 human volunteers, of whom 81 were eligible for the statistical analysis.

Following oral administration of either the tablet or capsule (in the fasted state), tizanidine has peak plasma concentrations occurring 1.0 hours after dosing with a half-life of approximately 2 hours.

When two 4 mg tablets are administered with food the mean maximal plasma concentration is increased by approximately 30%, and the median time to peak plasma concentration is increased by 25 minutes, to 1 hour and 25 minutes.

In contrast, when two 4 mg capsules are administered with food the mean maximal plasma concentration is decreased by 20%, the median time to peak plasma concentration is increased by 2 hours to 3 hours. Consequently, the mean Cmax for the capsule when administered with food is approximately 2/3's the Cmax for the tablet when administered with food.

Food also increases the extent of absorption for both the tablets and capsules. The increase with the tablet (~30%) is significantly greater than with the capsule (~10%). Consequently when each is administered with food, the amount absorbed from the capsule is about 80% of the amount absorbed from the tablet (see Figure 1). Administration of the capsule contents sprinkled on applesauce is not bioequivalent to administration of an intact capsule under fasting conditions. Administration of the capsule contents on applesauce results in a 15% - 20% increase in Cmax and AUC of tizanidine compared to administration of an intact capsule while fasting, and a 15 minute decrease in the median lag time and time to peak concentration.

Figure 1: Mean Tizanidine Concentration vs. Time Profiles For Zanaflex Tablets and Capsules (2 × 4 mg) Under Fasted and Fed Conditions

SPECIAL POPULATIONS

Age Effects

No specific pharmacokinetic study was conducted to investigate age effects. Cross study comparison of pharmacokinetic data following single dose administration of 6 mg tizanidine showed that younger subjects cleared the drug four times faster than the elderly subjects. Tizanidine has not been evaluated in children (see PRECAUTIONS).

Hepatic Impairment

The influence of hepatic impairment on the pharmacokinetics of tizanidine has not been evaluated. Because tizanidine is extensively metabolized in the liver, hepatic impairment would be expected to have significant effects on pharmacokinetics of tizanidine. Tizanidine should ordinarily be avoided or used with extreme caution in this patient population (see WARNINGS).

Renal Impairment

Tizanidine clearance is reduced by more than 50% in elderly patients with renal insufficiency (creatinine clearance less than 25 mL/min) compared to healthy elderly subjects; this would be expected to lead to a longer duration of clinical effect. Tizanidine should be used with caution in renally impaired patients (see PRECAUTIONS).

Gender Effects

No specific pharmacokinetic study was conducted to investigate gender effects. Retrospective analysis of pharmacokinetic data, however, following single and multiple dose administration of 4 mg tizanidine showed that gender had no effect on the pharmacokinetics of tizanidine.

Race Effects

Pharmacokinetic differences due to race have not been studied.

DRUG INTERACTIONS

Fluvoxamine

The effect of fluvoxamine on the pharmacokinetics of tizanidine was studied in 10 healthy subjects. The Cmax, AUC, and half-life of tizanidine increased by 12-fold, 33-fold, and 3-fold, respectively. These changes resulted in significant decreases in blood pressure, increased drowsiness, and psychomotor impairment. (See CONTRAINDICATIONS and WARNINGS.)

Ciprofloxacin

The effect of ciprofloxacin on the pharmacokinetics of tizanidine was studied in 10 healthy subjects. The Cmax and AUC of tizanidine increased by 7-fold and 10-fold, respectively. These changes resulted in significant decreases in blood pressure, increased drowsiness, and psychomotor impairment. (See CONTRAINDICATIONS and WARNINGS.)

CYP1A2 Inhibitors

The interaction between tizanidine and either fluvoxamine or ciprofloxacin is most likely due to inhibition of CYP1A2 by fluvoxamine or ciprofloxacin. Although there have been no clinical studies evaluating the effects of other CYP1A2 inhibitors on tizanidine, other CYP1A2 inhibitors, such as zileuton, other fluoroquinolones, antiarrythmics (amiodarone, mexiletine, propafenone and verapamil), cimetidine, famotidine oral contraceptives, acyclovir and ticlopidine, may also lead to substantial increases in tizanidine blood concentrations (see WARNINGS).

Oral Contraceptives

No specific pharmacokinetic study was conducted to investigate interaction between oral contraceptives and tizanidine. Retrospective analysis of population pharmacokinetic data following single and multiple dose administration of 4 mg tizanidine, however, showed that women concurrently taking oral contraceptives had 50% lower clearance of tizanidine compared to women not on oral contraceptives (see PRECAUTIONS).

CLINICAL STUDIES

Tizanidine's capacity to reduce increased muscle tone associated with spasticity was demonstrated in two adequate and well controlled studies in patients with multiple sclerosis or spinal cord injury.

In one study, patients with multiple sclerosis were randomized to receive single oral doses of drug or placebo. Patients and assessors were blind to treatment assignment and efforts were made to reduce the likelihood that assessors would become aware indirectly of treatment assignment (e.g., they did not provide direct care to patients and were prohibited from asking questions about side effects). In all, 140 patients received either placebo, 8 mg or 16 mg of tizanidine.

Response was assessed by physical examination; muscle tone was rated on a 5 point scale (Ashworth score), with a score of 0 used to describe normal muscle tone. A score of 1 indicated a slight spastic catch while a score of 2 indicated more marked muscle resistance. A score of 3 was used to describe considerable increase in tone, making passive movement difficult. A muscle immobilized by spasticity was given a score of 4. Spasm counts were also collected.

Assessments were made at 1, 2, 3 and 6 hours after treatment. A statistically significant reduction of the Ashworth score for Zanaflex compared to placebo was detected at 1, 2 and 3 hours after treatment. Figure 2 below shows a comparison of the mean change in muscle tone from baseline as measured by the Ashworth scale. The greatest reduction in muscle tone was 1 to 2 hours after treatment. By 6 hours after treatment, muscle tone in the 8 and 16 mg tizanidine groups was indistinguishable from muscle tone in placebo treated patients. Within a given patient, improvement in muscle tone was correlated with plasma concentration. Plasma concentrations were variable from patient to patient at a given dose. Although 16 mg produced a larger effect, adverse events including hypotension were more common and more severe than in the 8 mg group. There were no differences in the number of spasms occurring in each group.

Figure 2: Single Dose Study—Mean Change in Muscle Tone from Baseline as Measured by the Ashworth Scale ± 95% Confidence Interval (A Negative Ashworth Score Signifies an Improvement in Muscle Tone from Baseline)

In a multiple dose study, 118 patients with spasticity secondary to spinal cord injury were randomized to either placebo or tizanidine. Steps similar to those taken in the first study were employed to ensure the integrity of blinding.

Patients were titrated over 3 weeks up to a maximum tolerated dose or 36 mg daily given in three unequal doses (e.g., 10 mg given in the morning and afternoon and 16 mg given at night). Patients were then maintained on their maximally tolerated dose for 4 additional weeks (i.e., maintenance phase). Throughout the maintenance phase, muscle tone was assessed on the Ashworth scale within a period of 2.5 hours following either the morning or afternoon dose. The number of daytime spasms was recorded daily by patients.

At endpoint (the protocol-specified time of outcome assessment), there was a statistically significant reduction in muscle tone and frequency of spasms in the tizanidine treated group compared to placebo. The reduction in muscle tone was not associated with a reduction in muscle strength (a desirable outcome) but also did not lead to any consistent advantage of tizanidine treated patients on measures of activities of daily living. Figure 3 below shows a comparison of the mean change in muscle tone from baseline as measured by the Ashworth scale.

Figure 3: Multiple Dose Study—Mean Change in Muscle Tone 0.5–2.5 Hours After Dosing as Measured by the Ashworth Scale ± 95% Confidence Interval (A Negative Ashworth Score Signifies an Improvement in Muscle Tone from Baseline)

INDICATIONS AND USAGE

Tizanidine is a short-acting drug for the management of spasticity. Because of the short duration of effect, treatment with tizanidine should be reserved for those daily activities and times when relief of spasticity is most important (see DOSAGE AND ADMINISTRATION).

CONTRAINDICATIONS

Concomitant use of tizanidine with fluvoxamine or with ciprofloxacin, potent inhibitors of CYP1A2, is contraindicated. Significant alterations of pharmacokinetic parameters of tizanidine including increased AUC, t1/2, Cmax, increased oral bioavailability and decreased plasma clearance have been observed with concomitant administration of either fluvoxamine or ciprofloxacin. This pharmacokinetic interaction can result in potentially serious adverse events (See WARNINGS and CLINICAL PHARMACOLOGY: Drug Interactions).

Zanaflex is contraindicated in patients with known hypersensitivity to Zanaflex or its ingredients.

WARNINGS

LIMITED DATA BASE FOR CHRONIC USE OF SINGLE DOSES ABOVE 8 MG AND MULTIPLE DOSES ABOVE 24 MG PER DAY

Clinical experience with long-term use of tizanidine at doses of 8 to 16 mg single doses or total daily doses of 24 to 36 mg (see DOSAGE AND ADMINISTRATION) is limited. In safety studies, approximately 75 patients have been exposed to individual doses of 12 mg or more for at least one year or more and approximately 80 patients have been exposed to total daily doses of 30 to 36 mg/day for at least one year or more. There is essentially no long-term experience with single, daytime doses of 16 mg. Because long-term clinical study experience at high doses is limited, only those adverse events with a relatively high incidence are likely to have been identified (see WARNINGS, PRECAUTIONS and ADVERSE REACTIONS).

HYPOTENSION

Tizanidine is an α2-adrenergic agonist (like clonidine) and can produce hypotension. In a single dose study where blood pressure was monitored closely after dosing, two-thirds of patients treated with 8 mg of tizanidine had a 20% reduction in either the diastolic or systolic BP. The reduction was seen within 1 hour after dosing, peaked 2 to 3 hours after dosing and was associated, at times, with bradycardia, orthostatic hypotension, lightheadedness/dizziness and rarely syncope. The hypotensive effect is dose related and has been measured following single doses of ≥ 2 mg.

The chance of significant hypotension may possibly be minimized by titration of the dose and by focusing attention on signs and symptoms of hypotension prior to dose advancement. In addition, patients moving from a supine to fixed upright position may be at increased risk for hypotension and orthostatic effects.

Caution is advised when tizanidine is to be used in patients receiving concurrent antihypertensive therapy and should not be used with other α2-adrenergic agonists.

Clinically significant hypotension (decreases in both systolic and diastolic pressure) has been reported with concomitant administration of either fluvoxamine or ciprofloxacin and single doses of 4 mg of tizanidine. Therefore, concomitant use of tizanidine with fluvoxamine or with ciprofloxacin, potent inhibitors of CYP1A2, is contraindicated (see CONTRAINDICATIONS and CLINICAL PHARMACOLOGY: Drug Interactions).

RISK OF LIVER INJURY

Tizanidine occasionally causes liver injury, most often hepatocellular in type. In controlled clinical studies, approximately 5% of patients treated with tizanidine had elevations of liver function tests (ALT/SGPT, AST/SGOT) to greater than 3 times the upper limit of normal (or 2 times if baseline levels were elevated) compared to 0.4% in the control patients. Most cases resolved rapidly upon drug withdrawal with no reported residual problems. In occasional symptomatic cases, nausea, vomiting, anorexia and jaundice have been reported. Based upon postmarketing experience, death associated with liver failure has been a rare occurrence reported in patients treated with tizanidine.

Monitoring of aminotransferase levels is recommended during the first 6 months of treatment (e.g., baseline, 1, 3 and 6 months) and periodically thereafter, based on clinical status. Because of the potential toxic hepatic effect of tizanidine, the drug should ordinarily be avoided or used with extreme caution in patients with impaired hepatic function.

SEDATION

In the multiple dose, controlled clinical studies, 48% of patients receiving any dose of tizanidine reported sedation as an adverse event. In 10% of these cases, the sedation was rated as severe compared to less than 1% in the placebo treated patients. Sedation may interfere with everyday activity.

The effect appears to be dose related. In a single dose study, 92% of the patients receiving 16 mg, when asked, reported that they were drowsy during the 6 hour study. This compares to 76% of the patients on 8 mg and 35% of the patients on placebo. Patients began noting this effect 30 minutes following dosing. The effect peaked 1.5 hours following dosing. Of the patients who received a single dose of 16 mg, 51% continued to report drowsiness 6 hours following dosing compared to 13% in the patients receiving placebo or 8 mg of tizanidine.

In the multiple dose studies, the prevalence of patients with sedation peaked following the first week of titration and then remained stable for the duration of the maintenance phase of the study.

HALLUCINOSIS/PSYCHOTIC-LIKE SYMPTOMS

Tizanidine use has been associated with hallucinations. Formed, visual hallucinations or delusions have been reported in 5 of 170 patients (3%) in two North American controlled clinical studies. These 5 cases occurred within the first 6 weeks. Most of the patients were aware that the events were unreal. One patient developed psychoses in association with the hallucinations. One patient among these 5 continued to have problems for at least 2 weeks following discontinuation of tizanidine.

USE IN PATIENTS WITH HEPATIC IMPAIRMENT

The influence of hepatic impairment on the pharmacokinetics of tizanidine has not been evaluated. Because tizanidine is extensively metabolized in the liver, hepatic impairment would be expected to have significant effects on the pharmacokinetics of tizanidine. Tizanidine should ordinarily be avoided or used with extreme caution in patients with hepatic impairment (see also RISK OF LIVER INJURY).

POTENTIAL INTERACTION WITH FLUVOXAMINE OR CIPROFLOXACIN

In a pharmacokinetic study, tizanidine serum concentration was significantly increased (Cmax 12-fold, AUC 33-fold) when the drug was given concomitantly with fluvoxamine. Potentiated hypotensive and sedative effects were observed. Fluvoxamine and tizanidine should not be used together. (See CONTRAINDICATIONS and CLINICAL PHARMACOLOGY: Drug Interactions.)

In a pharmacokinetic study, tizanidine serum concentration was significantly increased (Cmax 7-fold, AUC 10-fold) when the drug was given concomitantly with ciprofloxacin. Potentiated hypotensive and sedative effects were observed. Ciprofloxacin and tizanidine should not be used together (see CONTRAINDICATIONS and CLINICAL PHARMACOLOGY: Drug Interactions).

POSSIBLE INTERACTION WITH OTHER CYP1A2 INHIBITORS

Because of potential drug interactions, concomitant use of tizanidine with other CYP1A2 inhibitors, such as zileuton, other fluoroquinolones, antiarrythmics (amiodarone, mexiletine, propafenone, and verapamil), cimetidine, famotidine, oral contraceptives, acyclovir and ticlopidine (see CLINICAL PHARMACOLOGY: Drug Interactions) should ordinarily be avoided. If their use is clinically necessary, they should be used with caution.

PRECAUTIONS

CARDIOVASCULAR

Prolongation of the QT interval and bradycardia were noted in chronic toxicity studies in dogs at doses equal to the maximum human dose on a mg/m^2 basis. ECG evaluation was not performed in the controlled clinical studies. Reduction in pulse rate has been noted in association with decreases in blood pressure in the single dose controlled study (see WARNINGS).

OPHTHALMIC

Dose-related retinal degeneration and corneal opacities have been found in animal studies at doses equivalent to approximately the maximum recommended dose on a mg/m^2 basis. There have been no reports of corneal opacities or retinal degeneration in the clinical studies.

USE IN RENALLY IMPAIRED PATIENTS

Tizanidine should be used with caution in patients with renal insufficiency (creatinine clearance less than 25 mL/min), as clearance is reduced by more than 50%. In these patients, during titration, the individual doses should be reduced. If higher doses are required, individual doses rather than dosing frequency should be increased. These patients should be monitored closely for the onset or increase in severity of the common adverse events (dry mouth, somnolence, asthenia and dizziness) as indicators of potential overdose.

USE IN WOMEN TAKING ORAL CONTRACEPTIVES

Because drug interaction studies of tizanidine with oral contraceptives have shown that concomitant use may reduce the clearance of tizanidine by as much as 50%, concomitant use of tizanidine with oral contraceptives should ordinarily be avoided (see CLINICAL PHARMACOLOGY: Drug Interactions). However, if concomitant use is clinically necessary, the starting dose and subsequent titration rate of tizanidine should be reduced.

DISCONTINUING THERAPY

If therapy needs to be discontinued, particularly in patients who have been receiving high doses for long periods, the dose should be decreased slowly to minimize the risk of withdrawal and rebound hypertension, tachycardia, and hypertonia.

INFORMATION FOR PATIENTS

Patients should be advised of the limited clinical experience with tizanidine both in regard to duration of use and the higher doses required to reduce muscle tone (see WARNINGS).

Because of the possibility of tizanidine lowering blood pressure, patients should be warned about the risk of clinically significant orthostatic hypotension (see WARNINGS).

Because of the possibility of sedation, patients should be warned about performing activities requiring alertness, such as driving a vehicle or operating machinery (see WARNINGS). Patients should also be instructed that the sedation may be additive when tizanidine is taken in conjunction with drugs (baclofen, benzodiazepines) or substances (e.g., alcohol) that act as CNS depressants.

Patients should be advised of the change in the absorption profile of tizanidine if taken with food and the potential changes in efficacy and adverse effect profiles that may result (see CLINICAL PHARMACOLOGY: Pharmacokinetics).

Patients should be advised not to stop tizanidine suddenly as rebound hypertension and tachycardia may occur (see PRECAUTIONS: Discontinuing Therapy).

Tizanidine should be used with caution where spasticity is utilized to sustain posture and balance in locomotion or whenever spasticity is utilized to obtain increased function.

Because of the potential for the increased risk of serious adverse reactions including severe lowering of blood pressure and sedation when tizanidine and either fluvoxamine or ciprofloxacin are used together, tizanidine should not be used with either fluvoxamine or ciprofloxacin. Because of the potential for interaction with other CYP1A2 inhibitors, patients should be instructed to inform their physicians and pharmacists when any medication is added or removed from their regimen.

DRUG INTERACTIONS

In vitro studies of cytochrome P450 isoenzymes using human liver microsomes indicate that neither tizanidine nor the major metabolites are likely to affect the metabolism of other drugs metabolized by cytochrome P450 isoenzymes.

Fluvoxamine

The effect of fluvoxamine on the pharmacokinetics of a single 4 mg dose of tizanidine was studied in 10 healthy subjects. The Cmax, AUC, and half-life of tizanidine increased by 12-fold, 33-fold, and 3-fold, respectively. These changes resulted in significantly decreased blood pressure, increased drowsiness, and increased psychomotor impairment. (See CONTRAINDICATIONS and WARNINGS.)

Ciprofloxacin

The effect of ciprofloxacin on the pharmacokinetics of a single 4 mg dose of tizanidine was studied in 10 healthy subjects. The Cmax and AUC of tizanidine increased by 7-fold and 10-fold, respectively. These changes resulted in significantly decreased blood pressure, increased drowsiness, and increased psychomotor impairment. (See CONTRAINDICATIONS and WARNINGS.)

CYP1A2 inhibitors

The interaction between tizanidine and either fluvoxamine or ciprofloxacin is most likely due to inhibition of CYP1A2 by fluvoxamine or ciprofloxacin. Although there have been no clinical studies evaluating the effects of other CYP1A2 inhibitors on tizanidine, other CYP1A2 inhibitors, including zileuton, other fluroquinolones, antiarrythmics (amiodarone, mexiletine, propafenone, and verapamil), cimetidine and famotidine, oral contraceptives, acyclovir, and ticlopidine may also lead to substantial increases in tizanidine blood concentrations. Concomitant use of tizanidine with CYP1A2 inhibitors should ordinarily be avoided. If their use is clinically necessary, they should be used with caution (see WARNINGS).

Acetaminophen

Tizanidine delayed the Tmax of acetaminophen by 16 minutes. Acetaminophen did not affect the pharmacokinetics of tizanidine.

Alcohol

Alcohol increased the AUC of tizanidine by approximately 20%, while also increasing its Cmax by approximately 15%. This was associated with an increase in side effects of tizanidine. The CNS depressant effects of tizanidine and alcohol are additive.

Oral Contraceptives

No specific pharmacokinetic study was conducted to investigate interaction between oral contraceptives and tizanidine, but retrospective analysis of population pharmacokinetic data following single and multiple dose administration of 4 mg tizanidine showed that women concurrently taking oral contraceptives had 50% lower clearance of tizanidine that women not on oral contraceptives.

CARCINOGENESIS, MUTAGENESIS, IMPAIRMENT OF FERTILITY

No evidence for carcinogenicity was seen in two dietary studies in rodents. Tizanidine was administered to mice for 78 weeks at doses up to 16 mg/kg, which is equivalent to 2 times the maximum recommended human dose on a mg/m^2 basis. Tizanidine was also administered to rats for 104 weeks at doses up to 9 mg/kg, which is equivalent to 2.5 times the maximum recommended human dose on a mg/m^2 basis. There was no statistically significant increase in tumors in either species.

Tizanidine was not mutagenic or clastogenic in the following in vitro assays: the bacterial Ames test and the mammalian gene mutation test and chromosomal aberration test in Chinese hamster cells. It was also negative in the following in vivo assays: the bone marrow micronucleus test in mice, the bone marrow micronucleus and cytogenicity test in Chinese hamsters, the dominant lethal mutagenicity test in mice, and the unscheduled DNA synthesis (UDS) test in mice.

Tizanidine did not affect fertility in male rats at doses of 10 mg/kg, approximately 2.7 times the maximum recommended human dose on a mg/m^2 basis, and in females at doses of 3 mg/kg, approximately equal to the maximum recommended human dose on a mg/m^2 basis; fertility was reduced in males receiving 30 mg/kg (8 times the maximum recommended human dose on a mg/m2 basis) and in females receiving 10 mg/kg (2.7 times the maximum recommended human dose on a mg/m^2 basis). At these doses, maternal behavioral effects and clinical signs were observed including marked sedation, weight loss, and ataxia.

PREGNANCY

Pregnancy Category C

Reproduction studies performed in rats at a dose of 3 mg/kg, equal to the maximum recommended human dose on a mg/m^2 basis, and in rabbits at 30 mg/kg, 16 times the maximum recommended human dose on a mg/m^2 basis, did not show evidence of teratogenicity. Tizanidine at doses that are equal to and up to 8 times the maximum recommended human dose on a mg/m^2 basis increased gestation duration in rats. Prenatal and postnatal pup loss was increased and developmental retardation occurred. Post-implantation loss was increased in rabbits at doses of 1 mg/kg or greater, equal to or greater than 0.5 times the maximum recommended human dose on a mg/m^2 basis. Tizanidine has not been studied in pregnant women. Tizanidine should be given to pregnant women only if clearly needed.

LABOR AND DELIVERY

The effect of tizanidine on labor and delivery in humans is unknown.

NURSING MOTHERS

It is not known whether tizanidine is excreted in human milk, although as a lipid soluble drug, it might be expected to pass into breast milk.

GERIATRIC USE

Tizanidine should be used with caution in elderly patients because clearance is decreased four-fold.

PEDIATRIC USE

There are no adequate and well-controlled studies to document the safety and efficacy of tizanidine in children.

ADVERSE REACTIONS

In multiple dose, placebo-controlled clinical studies, 264 patients were treated with tizanidine and 261 with placebo. Adverse events, including severe adverse events, were more frequently reported with tizanidine than with placebo.

COMMON ADVERSE EVENTS LEADING TO DISCONTINUATION

Forty-five of 264 (17%) patients receiving tizanidine and 13 of 261 (5%) of patients receiving placebo in three multiple dose, placebo-controlled clinical studies, discontinued treatment for adverse events. When patients withdrew from the study, they frequently had more than one reason for discontinuing. The adverse events most frequently leading to withdrawal of tizanidine treated patients in the controlled clinical studies were asthenia (weakness, fatigue and/or tiredness) (3%), somnolence (3%), dry mouth (3%), increased spasm or tone (2%), and dizziness (2%).

MOST FREQUENT ADVERSE CLINICAL EVENTS SEEN IN ASSOCIATION WITH THE USE OF TIZANIDINE

In multiple dose, placebo-controlled clinical studies involving 264 patients with spasticity, the most frequent adverse effects were dry mouth, somnolence/sedation, asthenia (weakness, fatigue and/or tiredness) and dizziness. Three-quarters of the patients rated the events as mild to moderate and one-quarter of the patients rated the events as being severe. These events appeared to be dose related.

ADVERSE EVENTS REPORTED IN CONTROLLED STUDIES

The events cited reflect experience gained under closely monitored conditions of clinical studies in a highly selected patient population. In actual clinical practice or in other clinical studies, these frequency estimates may not apply, as the conditions of use, reporting behavior, and the kinds of patients treated may differ. Table 1 lists treatment emergent signs and symptoms that were reported in greater than 2% of patients in three multiple dose, placebo-controlled studies who received tizanidine where the frequency in the tizanidine group was at least as common as in the placebo group. These events are not necessarily related to tizanidine treatment. For comparison purposes, the corresponding frequency of the event (per 100 patients) among placebo treated patients is also provided.
Table 1: Multiple Dose, Placebo-Controlled Studies—Frequent (> 2%) Adverse Events Reported for Which Tizanidine Tablets Incidence is Greater than Placebo

Event | Placebo N = 261 % | Zanaflex Tablet N = 264 %
Dry Mouth | 10 | 49
Somnolence | 10 | 48
Asthenia * | 16 | 41
Dissiness | 4 | 16
UTI | 7 | 10
Infection | 5 | 6
Constipation | 1 | 4
Liver function test abnormal | less than 1 | 3
Vomiting | 0 | 3
Speech Disorder | 0 | 3
Amblyopia (blurred vision) | less than 1 | 3
Urinary frequency | 2 | 3
Flu syndrome | 2 | 3
SGPT/ALT increased | less than 1 | 3
Dyskinesia | 0 | 3
Nervousness | less than 1 | 3
Pharyngitis | 1 | 3
Rhinitis | 2 | 3

* (weakness, fatigue, and/or tiredness)
In the single dose, placebo-controlled study involving 142 patients with spasticity, the patients were specifically asked if they had experienced any of the four most common adverse events: dry mouth, somnolence (drowsiness), asthenia (weakness, fatigue and/or tiredness) and dizziness. In addition, hypotension and bradycardia were observed. The occurrence of these adverse effects is summarized in Table 2. Other events were, in general, reported at a rate of 2% or less.
Table 2: Single Dose, Placebo-Controlled Study—Common Adverse Events Reported

Event | Placebo N = 48 % | Tizanidine Tablet 8mg,N = 45 | Tizanidine Tablet 16mg, N = 49
Somnolence | 31 | 78 | 92
Dry Mouth | 35 | 76 | 88
Asthenia * | 40 | 67 | 78
Dissiness | 4 | 22 | 45
Hypotension | 0 | 16 | 33
Bradycardia | 0 | 2 | 10

*(weakness, fatigue, and/or tiredness)

OTHER ADVERSE EVENTS OBSERVED DURING THE EVALUATION OF TIZANIDINE

Tizanidine was administered to 1385 patients in additional clinical studies where adverse event information was available. The conditions and duration of exposure varied greatly, and included (in overlapping categories) double-blind and open-label studies, uncontrolled and controlled studies, inpatient and outpatient studies, and titration studies. Untoward events associated with this exposure were recorded by clinical investigators using terminology of their own choosing. Consequently, it is not possible to provide a meaningful estimate of the proportion of individuals experiencing adverse events without first grouping similar types of untoward events into a smaller number of standardized event categories.

In the tabulations that follow, reported adverse events were classified using a standard COSTART-based dictionary terminology. The frequencies presented, therefore, represent the proportion of the 1385 patients exposed to tizanidine who experienced an event of the type cited on at least one occasion while receiving tizanidine. All reported events are included except those already listed in Table 1. If the COSTART term for an event was so general as to be uninformative, it was replaced by a more informative term. It is important to emphasize that, although the events reported occurred during treatment with tizanidine, they were not necessarily caused by it.

Events are further categorized by body system and listed in order of decreasing frequency according to the following definitions: frequent adverse events are those occurring on one or more occasions in at least 1/100 patients (only those not already listed in the tabulated results from placebo-controlled studies appear in this listing); infrequent adverse events are those occurring in 1/100 to 1/1000 patients; rare adverse events are those occurring in fewer than 1/1000 patients.

BODY AS A WHOLE
Frequent: | Fever
Infrequent: | Allergic reaction, moniliasis, malaise, abscess, neck pain, sepsis, cellulites, death, overdose
Rare: | Carcinoma, congenital anomaly, suicide attempt

CARDIOVASCULAR SYSTEM
Infrequent: | Vasodilatation, postural hypotension, syncope, migraine, arrhythmia
Rare: | Angina pectoris, coronary artery disorder, heart failure, myocardial infarct, phlebitis, pulmonary embolus, ventricular extrasystoles, ventricular tachycardia

DIGESTIVE SYSTEM
Frequent: | Abdomen pain, diarrhea, dyspepsia
Infrequent: | Dysphagia, cholelithiasis, fecal impaction, flatulence, gastrointestinal hemorrhage, hepatitis, melena,
Rare: | Gastroenteritis, hematemesis, hepatoma, intestinal obstruction, liver damage

HEMIC AND LYMPHATIC SYSTEM
Infrequent: | Ecchymosis, hypercholesteremia, anemia, hyperlipemia, leukopenia, leukocytosis, sepsis
Rare: | Petechia, purpura, thrombocythemia, thrombocytopenia

METABOLIC AND NUTRITIONAL SYSTEM
Infrequent: | Edema, hypothyroidism, weight loss
Rare: | Adrenal cortex insufficiency, hyperglycemia, hypokalemia, hyponatremia, hypoproteinemia, respiratory acidosis

MUSCULOSKELETAL SYSTEM
Frequent: | Myasthenia, back pain
Infrequent: | Pathological fracture, arthralgia, arthritis, bursitis

NERVOUS SYSTEM
Frequent: | Depression, anxiety, paresthesia
Infrequent: | Tremor, emotional lability, convulsion, paralysis, thinking abnormal, vertigo, abnormal dreams, agitation, depersonalization, euphoria, migraine, stupor, dysautonomia, neuralgia
Rare: | Dementia, hemiplegia, neuropathy

RESPIRATORY SYSTEM
Infrequent: | Sinusitis, pneumonia, bronchitis
Rare: | Asthma

SKIN AND APPENDAGES
Frequent: | Rash, sweating, skin ulcer
Infrequent: | Pruritus, dry skin, acne, alopecia, urticaria
Rare: | Exfoliative dermatitis, herpes simplex, herpes zoster, skin carcinoma

SPECIAL SENSES
Infrequent: | Ear pain, tinnitus, deafness, glaucoma, conjunctivitis, eye pain, optic neuritis, otitis media, retinal hemorrhage, visual field defect
Rare: | Iritis, keratitis, optic atrophy

UROGENITAL SYSTEM
Infrequent: | Urinary urgency, cystitis, menorrhagia, pyelonephritis, urinary retention, kidney calculus, uterine fibroids enlarged, vaginal moniliasis, vaginitis
Rare: | Albuminuria, glycosuria, hematuria, metrorrhagia

DRUG ABUSE AND DEPENDENCE

Abuse potential was not evaluated in human studies. Rats were able to distinguish tizanidine from saline in a standard discrimination paradigm, after training, but failed to generalize the effects of morphine, cocaine, diazepam, or phenobarbital to tizanidine. Monkeys were shown to self-administer tizanidine in a dose-dependent manner, and abrupt cessation of tizanidine produced transient signs of withdrawal at doses > 35 times the maximum recommended human dose on a mg/m^2 basis. These transient withdrawal signs (increased locomotion, body twitching, and aversive behavior toward the observer) were not reversed by naloxone administration.

Tizanidine is closely related to clonidine, which is often abused in combination with narcotics and is known to cause symptoms of rebound upon abrupt withdrawal. Three cases of rebound symptoms on sudden withdrawal of tizanidine have been reported. The case reports suggest that these patients were also misusing narcotics. Withdrawal symptoms included hypertension, tachycardia, hypertonia, tremor, and anxiety. As with clonidine, withdrawal is expected to be more likely in cases where high doses are used, especially for prolonged periods.

OVERDOSAGE

A review of the safety surveillance database revealed cases of intentional and accidental tizanidine overdose. Some of the cases resulted in fatality and many of the intentional overdoses were with multiple drugs including CNS depressants. The clinical manifestations of tizanidine overdose were consistent with its known pharmacology. In the majority of cases a decrease in sensorium was observed including lethargy, somnolence, confusion and coma. Depressed cardiac function are also observed including most often bradycardia and hypotension. Respiratory depression is another common feature of tizanidine overdose.

Should overdose occur, basic steps to ensure the adequacy of an airway and the monitoring of cardiovascular and respiratory systems should be undertaken. In general, symptoms resolve within one to three days following discontinuation of tizanidine and administration of appropriate therapy. Due to the similar mechanism of action, symptoms and management of tizanidine overdose are similar to those following clonidine overdose. For the most recent information concerning the management of overdose, contact a poison control center.

DOSAGE AND ADMINISTRATION

A single dose of 8 mg of tizanidine reduces muscle tone in patients with spasticity for a period of several hours. The effect peaks at approximately 1 to 2 hours and dissipates between 3 to 6 hours. Effects are dose-related.

Although single doses of less than 8 mg have not been demonstrated to be effective in controlled clinical studies, the dose-related nature of tizanidine's common adverse events make it prudent to begin treatment with single oral doses of 4 mg. Increase the dose gradually (2 to 4 mg steps) to optimum effect (satisfactory reduction of muscle tone at a tolerated dose).

The dose can be repeated at 6 to 8 hour intervals, as needed, to a maximum of three doses in 24 hours. The total daily dose should not exceed 36 mg.

Experience with single doses exceeding 8 mg and daily doses exceeding 24 mg is limited. There is essentially no experience with repeated, single, daytime doses greater than 12 mg or total daily doses greater than 36 mg (see WARNINGS).

Food has complex effects on tizanidine pharmacokinetics, which differ with the different formulations. These pharmacokinetic differences may result in clinically significant differences when [1] switching administration of the tablet between the fed or fasted state, [2] switching administration of the capsule between the fed or fasted state, [3] switching between the tablet and capsule in the fed state, or [4] switching between the intact capsule and sprinkling the contents of the capsule on applesauce. These changes may result in increased adverse events or delayed/more rapid onset of activity, depending upon the nature of the switch. For this reason, the prescriber should be thoroughly familiar with the changes in kinetics associated with these different conditions (see CLINICAL PHARMACOLOGY: Pharmacokinetics).

HOW SUPPLIED

Zanaflex Capsules®

Zanaflex Capsules® (tizanidine hydrochloride) are available in three strengths as two-piece hard gelatin capsules containing tizanidine hydrochloride 2 mg, 4 mg or 6 mg. The 2 mg capsules have a standard blue opaque body with a standard blue opaque cap with "2 MG" printed on the cap. The 4 mg capsules have a white opaque body with a standard blue opaque cap with "4 MG" printed on the cap. The 6 mg capsules have a light blue opaque body with a white stripe and light blue opaque cap with "6 MG" printed on the capsules. The capsules are provided as follows:

Zanaflex Capsules® (tizanidine hydrochloride), 2 mg, bottles of 150 capsules (NDC 10144-602-15)
Zanaflex Capsules® (tizanidine hydrochloride), 4 mg, bottles of 150 capsules (NDC 10144-604-15)
Zanaflex Capsules® (tizanidine hydrochloride), 6 mg, bottles of 150 capsules (NDC 10144-606-15)

Store at 25°C (77°F); excursions permitted to 15–30°C (59–86°F) [see USP Controlled Room Temperature].

Dispense in containers with child resistant closure

Zanaflex® tablets

Zanaflex® (tizanidine hydrochloride) tablets are available in one strength as white, uncoated tablets containing tizanidine hydrochloride 4 mg. The 4 mg tablets have a quadrisecting score on one side and are debossed with "A594" on the other side. Tablets are provided as follows:

Zanaflex® (tizanidine hydrochloride) tablets, 4 mg, bottles of 150 tablets (NDC 10144-594-15)

Store at 25°C (77°F); excursions permitted to 15–30°C (59–86°F) [see USP Controlled Room Temperature].

Dispense in containers with child resistant closure

Rx Only

Zanaflex® is the registered trademark of Acorda Therapeutics, Inc. Zanaflex Capsules® is the trademark of Acorda Therapeutics, Inc.

Marketed and Distributed by:
Acorda Therapeutics, Inc.
Hawthorne, NY 10532

©2008, Acorda Therapeutics, Inc., All rights reserved.

Rev. 04/08